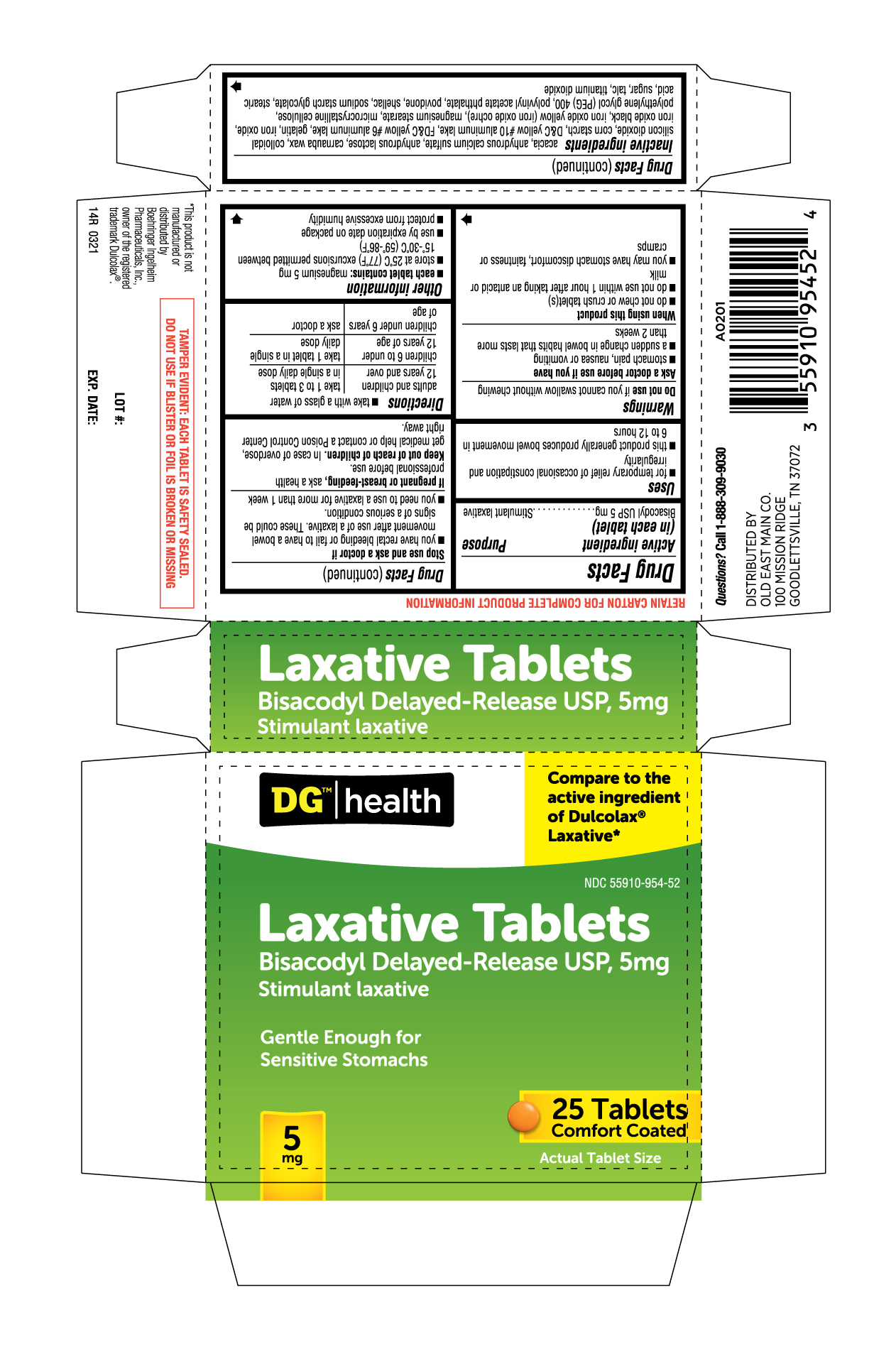 DRUG LABEL: Extra Gentle Laxative
NDC: 55910-954 | Form: TABLET, DELAYED RELEASE
Manufacturer: DOLGENCORP INC
Category: otc | Type: HUMAN OTC DRUG LABEL
Date: 20250210

ACTIVE INGREDIENTS: BISACODYL 5 mg/1 1
INACTIVE INGREDIENTS: CALCIUM SULFATE ANHYDROUS; STARCH, CORN; D&C YELLOW NO. 10 ALUMINUM LAKE; FD&C YELLOW NO. 6 ALUMINUM LAKE; SILICON DIOXIDE; POLYETHYLENE GLYCOL 400; ANHYDROUS LACTOSE; GELATIN; FERRIC OXIDE RED; FERROSOFERRIC OXIDE; MICROCRYSTALLINE CELLULOSE; SHELLAC; ACACIA; CARNAUBA WAX; FERRIC OXIDE YELLOW; MAGNESIUM STEARATE; POLYVINYL ACETATE PHTHALATE; POVIDONE; SODIUM STARCH GLYCOLATE TYPE A POTATO; STEARIC ACID; SUCROSE; TALC; TITANIUM DIOXIDE

14R Dollar General 55910 954 Bisacodyl Delayed-Release USP,5mg ct25

Active ingredient
(in each tablet)
Bisacodyl USP 5 mg

Purpose
Stimulant laxative

Uses

- for temporary relief of occasional constipation and irregularity
- this product generally produces bowel movement in 6 to 12 hours

Warnings

Do not use if you cannot swallow without chewing

Ask a doctor before use if you have

- stomach pain, nausea or vomiting
- a sudden change in bowel habits that lasts more than 2 weeks

When using this product

- do not chew or crush tablet(s)
- do not use within 1 hour after taking an antacid or milk
- you may have stomach discomtort, faintness or cramps

Stop use and ask a doctor if

- you have rectal bleeding or fail to have a bowel movement after use of a laxative. These could be signs of a serious condition.
- you need to use a laxative for more than 1 week

PREGNANCY OR BREAST FEEDING

If pregnant or breast-feeding, ask a health professional before use.

Keep out of reach of children. In case of overdose, get medical help or contact a Poison Control Center right away.

Directions

- take with a glass of water

adults and children 12 years and over: take 1 to 3 tablets in a single daily dose
children 6 to under 12 years of age: take 1 tablet in a single daily dose
children under 6 years of age:ask a doctor

OTHER INFORMATION

- each tablet contains: magnesium 5 mg
- store at 25^0C (77^0F) excursions permitted between 15^0C-30^0C (59^0-86^0F)
- use by expiration date on package
- protect from excessive humidity

INACTIVE INGREDIENT

Inactive ingredients acacia, anhydrous calcium sulfate, anhydrous lactose, carnauba wax, colloidal silicon dioxide, corn starch, D&C yellow #10 aluminum lake, FD&C yellow #6 aluminum lake, gelatin, iron oxide, iron oxide black, iron oxide yellow (iron oxide ochre), magnesium stearate, microcrystalline cellulose,
polyethylene glycol (PEG) 400, polyvinyl acetate phthalate, povidone, shellac, sodium starch glycolate, stearic acid, sugar, talc, titanium dioxide

Questions? Call 1-888-309-9030